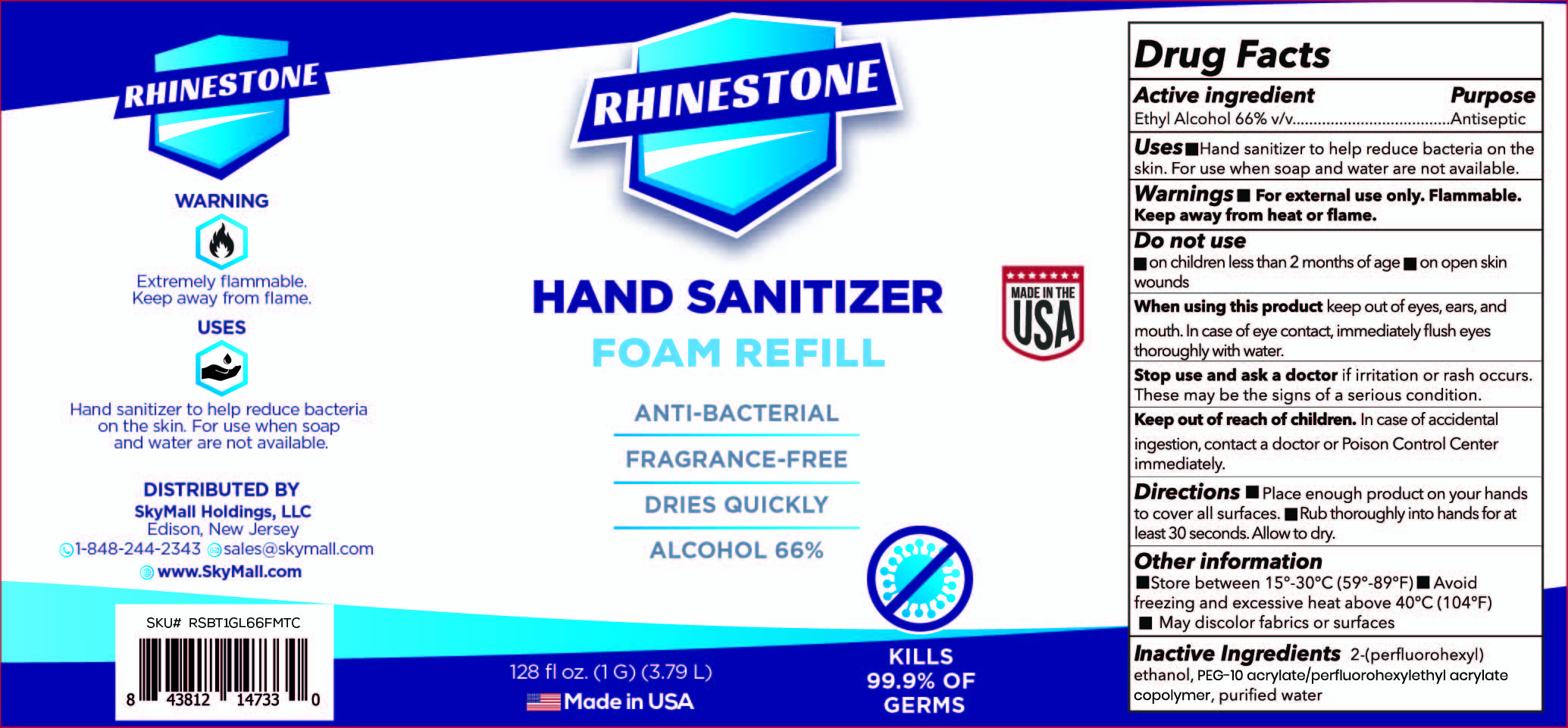 DRUG LABEL: Hand Sanitizer
NDC: 80230-001 | Form: LIQUID
Manufacturer: Skymall Holdings LLC
Category: otc | Type: HUMAN OTC DRUG LABEL
Date: 20200824

ACTIVE INGREDIENTS: ALCOHOL 66 mL/100 mL
INACTIVE INGREDIENTS: WATER; PEG-10 ACRYLATE/PERFLUOROHEXYLETHYL ACRYLATE COPOLYMER; 2-(PERFLUOROHEXYL)ETHANOL

Skymall Zink Brntag Rhinestone Foam Sanitizer Alc66

Active Ingredient

Alcohol 66%v/v

Purpose

Antiseptic

Uses

■ Hand sanitizer to help reduce bacteria on the skin. For use when soap and water are not available

Warnings

■ For external use only. Flammable. Keep away from heat or flame

Do not use

■ on children less than 2 months of age ■ on open skin wounds

When using this product

keep out of eyes, ears, ears and mouth. In case of eye contact immediately flush eyes thoroughly with water.

Stop use and ask a doctor

if irritation or rash occurs. These may be the signs of a serious condition.

Keep out of reach of children

In case of accidentail ingestion, contact a doctor or Poison Control Center immediately.

Directions

■ Place enough product on hands to cover all surfaces. ■ Rub thoroughly into hands for at least 30 seconds. Allow to dry.

Other information

■ Store between 15º-30ºC (59º-89ºF) ■ Avoid freezing and excessive heat above 40ºC (104ºF) ■ May discolor fabrics or surfaces.

Inactive ingredients

2-(perfluorohexyl)ethanol, PEG-10 acrylate/perfluorohexylethyl acrylate copolymer, purified water